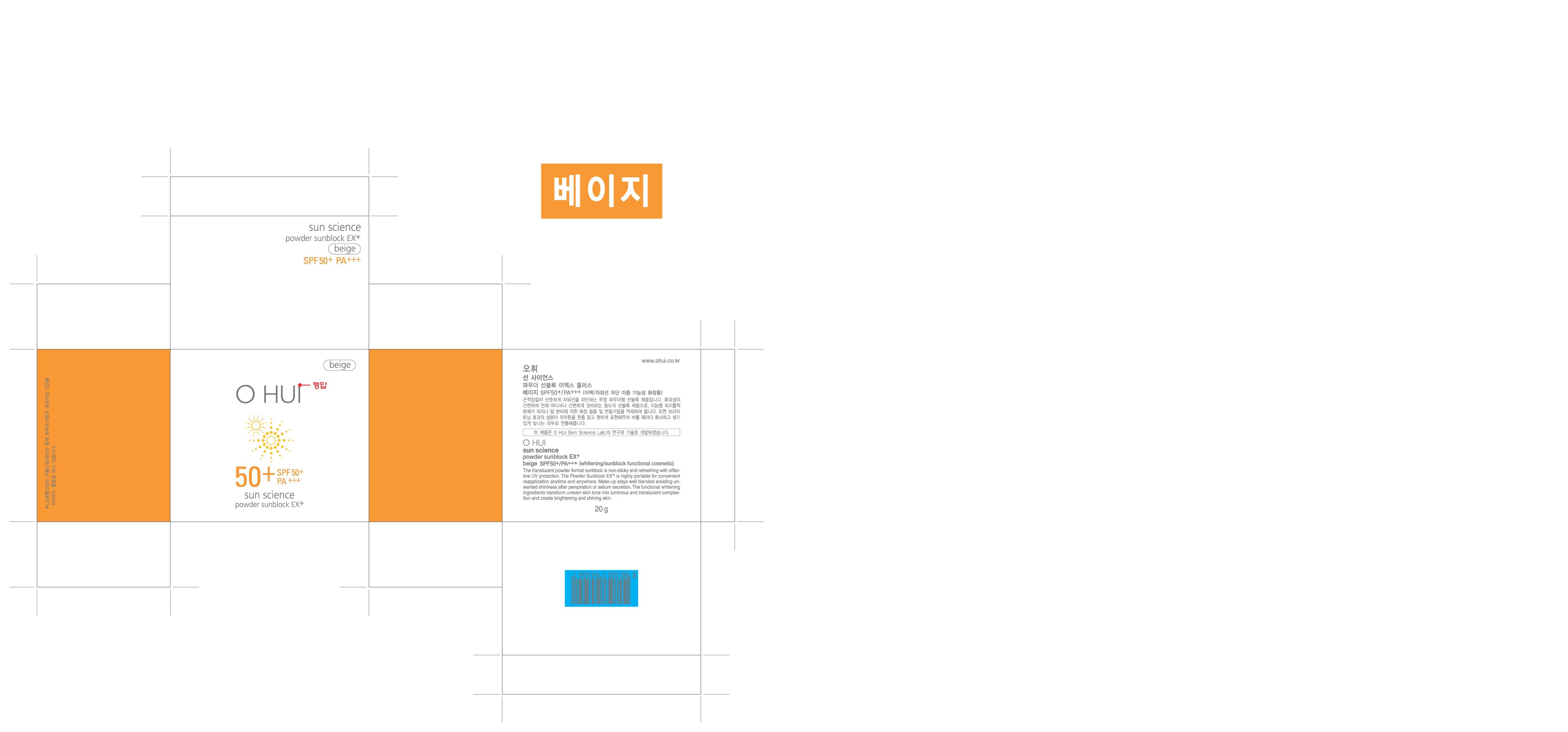 DRUG LABEL: OHUI Sun Science Sun Block EX plus Beige
NDC: 53208-524 | Form: POWDER
Manufacturer: LG Household and Healthcare, Inc.
Category: otc | Type: HUMAN OTC DRUG LABEL
Date: 20110525

ACTIVE INGREDIENTS: TALC 55.493 g/100 g; OCTINOXATE 7.2 g/100 g; ZINC OXIDE 5.76 g/100 g; TITANIUM DIOXIDE 2.59956 g/100 g; ARBUTIN 2 g/100 g; ATRACTYLODES JAPONICA ROOT OIL 0.1 g/100 g
INACTIVE INGREDIENTS: ALUMINUM HYDROXIDE; MICA; DIMETHICONE; SILICON DIOXIDE; ALUMINUM STARCH OCTENYLSUCCINATE; STEARIC ACID; WATER; ALCOHOL; METHYLPARABEN; FERRIC OXIDE YELLOW; FERRIC OXIDE RED; TRIBASIC CALCIUM PHOSPHATE; FERROSOFERRIC OXIDE; PROPYLPARABEN

Drug Fact

ACTIVE INGREDIENT

TALC 55.493%
OCTINOXATE 7.2%
ZINC OXIDE 5.76%
TITANIUM DIOXIDE 2.59956%
ARBUTIN 2%
ATRACTYLODES JAPONICA ROOT OIL 0.1%

WARNINGS AND PRECAUTIONS

For external use only.

Keep out of reach of children. Is swallowed, get medical help or contact a Poison Control Center right away

WHEN USING

Keep out of eyes. Rinse with water to remove.

PACKAGE LABEL

OH Sun Science Powder Sun Block EX plus_Beige